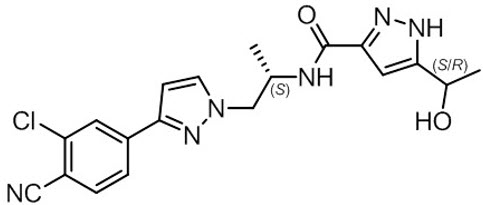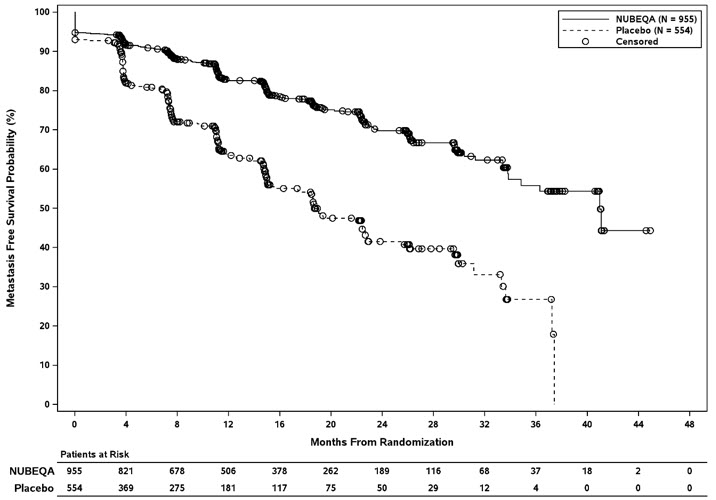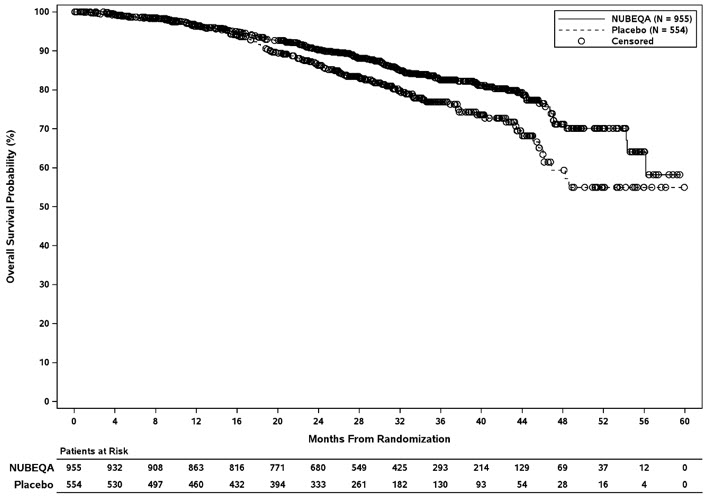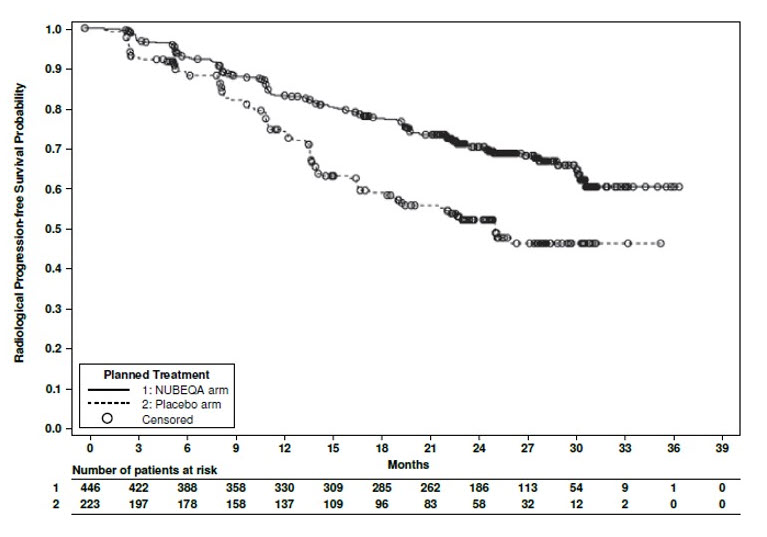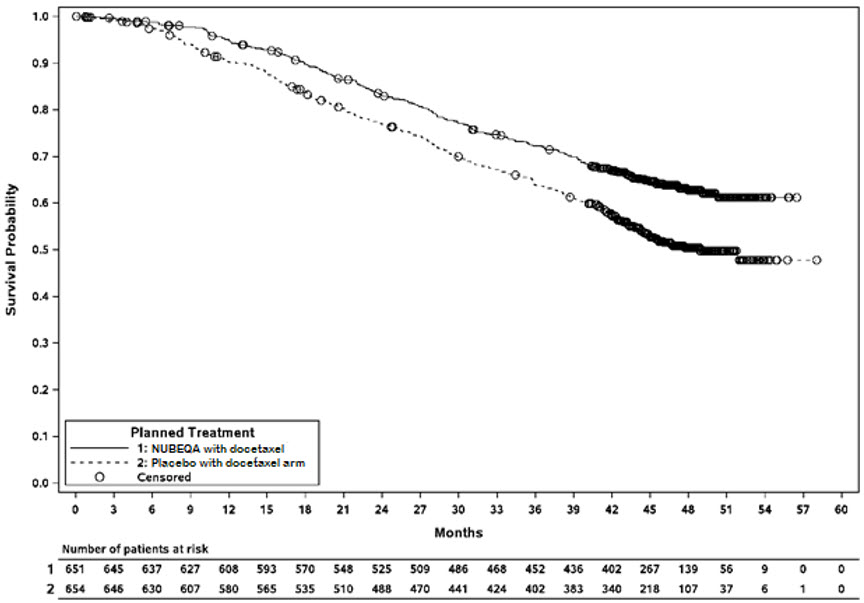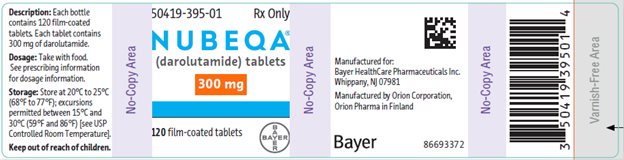 DRUG LABEL: NUBEQA
NDC: 50419-395 | Form: TABLET, FILM COATED
Manufacturer: Bayer HealthCare Pharmaceuticals Inc.
Category: prescription | Type: HUMAN PRESCRIPTION DRUG LABEL
Date: 20251029

ACTIVE INGREDIENTS: DAROLUTAMIDE 300 mg/1 1
INACTIVE INGREDIENTS: ANHYDROUS DIBASIC CALCIUM PHOSPHATE; CROSCARMELLOSE SODIUM; LACTOSE MONOHYDRATE; MAGNESIUM STEARATE; POVIDONE K30; POLYETHYLENE GLYCOL 3350; TITANIUM DIOXIDE

HIGHLIGHTS OF PRESCRIBING INFORMATION

These highlights do not include all the information needed to use NUBEQA safely and effectively. See full prescribing information for NUBEQA.
NUBEQA® (darolutamide) tablets, for oral use
Initial U.S. Approval: 2019

RECENT MAJOR CHANGES

Indications and Usage (1) | 6/2025
Dosage and Administration (2.1) | 6/2025
Warnings and Precautions (5.1, 5.2) | 6/2025

1 INDICATIONS AND USAGE

NUBEQA is an androgen receptor inhibitor indicated for the treatment of adult patients with:

- non-metastatic castration-resistant prostate cancer (nmCRPC). (1)
- metastatic castration-sensitive prostate cancer (mCSPC). (1)
- metastatic castration-sensitive prostate cancer (mCSPC) in combination with docetaxel. (1)

2 DOSAGE AND ADMINISTRATION

Recommended Dosage: NUBEQA 600 mg (two 300 mg tablets) administered orally twice daily. Swallow tablets whole. Take NUBEQA with food. (2.1)

For patients with mCSPC treated with NUBEQA in combination with docetaxel, administer the first cycle of docetaxel within 6 weeks after the start of NUBEQA treatment. (2.1)

Patients should also receive a gonadotropin-releasing hormone (GnRH) agonist or antagonist concurrently or have had bilateral orchiectomy. (2.1)

3 DOSAGE FORMS AND STRENGTHS

Tablets: 300 mg (3)

4 CONTRAINDICATIONS

None. (4)

5 WARNINGS AND PRECAUTIONS

- Ischemic Heart Disease: Optimize management of cardiovascular risk factors. Monitor for signs and symptoms of coronary artery disease. Discontinue NUBEQA for Grade 3-4 events. (5.1)
- Seizure: Consider discontinuation of NUBEQA in patients who develop a seizure during treatment. (5.2)
- Embryo-Fetal Toxicity: NUBEQA can cause fetal harm and loss of pregnancy. Advise males with female partners of reproductive potential to use effective contraception. (5.3, 8.1, 8.3)

6 ADVERSE REACTIONS

In nmCRPC and mCSPC: The most common adverse reactions (>10% with a ≥2% increase over placebo), including laboratory test abnormalities, are increased AST, decreased neutrophil count, increased bilirubin, fatigue, and increased ALT. (6.1)

In mCSPC in combination with docetaxel: The most common adverse reactions (≥10% with a ≥2% increase over placebo) are constipation, rash, decreased appetite, hemorrhage, increased weight, and hypertension.

The most common laboratory test abnormalities (≥30%) are anemia, hyperglycemia, decreased lymphocyte count, decreased neutrophil count, increased AST, increased ALT, and hypocalcemia. (6.1)

To report SUSPECTED ADVERSE REACTIONS, contact Bayer HealthCare Pharmaceuticals Inc. at 1-888-842-2937 or FDA at 1-800-FDA-1088 or WWW.FDA.GOV/MEDWATCH.

7 DRUG INTERACTIONS

- Combined P-gp and Strong or Moderate CYP3A Inducers: Avoid concomitant use. (7.1)
- Combined P-gp and Strong CYP3A Inhibitors: Monitor patients more frequently for NUBEQA adverse reactions. (7.1)
- BCRP Substrates: Avoid concomitant use with drugs that are BCRP substrates where possible. If used together, monitor patients more frequently for adverse reactions and consider dose reduction of the BCRP substrate drug. (7.2)
- OATP1B1 and OATP1B3 Substrates: Concomitant use of NUBEQA may increase the plasma concentrations of OATP1B1 or OATP1B3 substrates. If used together, monitor patients more frequently for adverse reactions and consider dose reduction of these drugs. (7.2)

8 USE IN SPECIFIC POPULATIONS

- Severe Renal Impairment (not on hemodialysis): Recommended dose is 300 mg twice daily. (8.6)
- Moderate Hepatic Impairment: Recommended dose is 300 mg twice daily. (8.7)

FULL PRESCRIBING INFORMATION

1 INDICATIONS AND USAGE

NUBEQA is indicated for the treatment of adult patients with:

- non-metastatic castration resistant prostate cancer (nmCRPC)
- metastatic castration-sensitive prostate cancer (mCSPC)
- metastatic castration-sensitive prostate cancer (mCSPC) in combination with docetaxel.

2 DOSAGE AND ADMINISTRATION

2.1 Recommended Dosage

The recommended dose of NUBEQA is 600 mg (two 300 mg tablets) taken orally, twice daily, with food [see Clinical Pharmacology (12.3)].

Continue treatment until disease progression or unacceptable toxicity occurs.

Patients receiving NUBEQA should also receive a gonadotropin-releasing hormone (GnRH) agonist or antagonist concurrently or have had a bilateral orchiectomy.

When used in combination with docetaxel for mCSPC, administer the first of 6 cycles of docetaxel within 6 weeks after the start of NUBEQA treatment. Refer to docetaxel prescribing information for additional dosing information, including dosage modifications. Treatment with NUBEQA may be continued until disease progression or unacceptable toxicity, even if a cycle of docetaxel is delayed, interrupted, or discontinued [see Dosage and Administration (2.2)].

Advise patients to swallow tablets whole with food, to take any missed dose as soon as they remember prior to the next scheduled dose, and not to take two doses together to make up for a missed dose.

2.2 Dosage Modification

If a patient experiences a greater than or equal to Grade 3 or an intolerable adverse reaction, withhold NUBEQA or reduce dosage to 300 mg twice daily until symptoms improve. NUBEQA may be resumed at a dose of 600 mg twice daily, when adverse reaction returns to baseline [see Adverse Reactions (6.1)]. Dosage reduction below 300 mg twice daily is not recommended.

For patients who experience ischemic heart disease or seizure, additional dose modifications may be required [see Warnings and Precautions (5.1 and 5.2)].

2.3 Recommended Dosage in Patients with Severe Renal Impairment

For patients with severe renal impairment (eGFR 15–29 mL/min/1.73 m^2) not receiving hemodialysis, the recommended dose of NUBEQA is 300 mg twice daily [see Use in Specific Populations (8.6) and Clinical Pharmacology (12.3)].

2.4 Recommended Dosage in Patients with Moderate Hepatic Impairment

For patients with moderate hepatic impairment (Child-Pugh Class B), the recommended dose of NUBEQA is 300 mg twice daily [see Use in Specific Populations (8.7) and Clinical Pharmacology (12.3)].

3 DOSAGE FORMS AND STRENGTHS

Tablets (300 mg): white to off-white oval film-coated tablets marked with "300" on one side and "Bayer" on the other.

4 CONTRAINDICATIONS

None.

5 WARNINGS AND PRECAUTIONS

5.1 Ischemic Heart Disease

Ischemic heart disease, including fatal cases, occurred in patients receiving NUBEQA.

In a pooled analysis of ARAMIS and ARANOTE, ischemic heart disease occurred in 3.4% of patients receiving NUBEQA and 2.2% receiving placebo, including Grade 3-4 events in 1.4% and 0.3%, respectively. Ischemic events led to death in 0.4% of patients receiving NUBEQA and 0.4% receiving placebo.

In ARASENS, ischemic heart disease occurred in 3.2% of patients receiving NUBEQA with docetaxel and 2% receiving placebo with docetaxel, including Grade 3-4 events in 1.3% and 1.1%, respectively. Ischemic events led to death in 0.3% of patients receiving NUBEQA with docetaxel and 0% receiving placebo with docetaxel.

Monitor for signs and symptoms of ischemic heart disease. Optimize management of cardiovascular risk factors, such as hypertension, diabetes, or dyslipidemia. Discontinue NUBEQA for Grade 3-4 ischemic heart disease.

5.2 Seizure

Seizure occurred in patients receiving NUBEQA.

In a pooled analysis of ARAMIS and ARANOTE, Grade 1-3 seizure occurred in 0.2% of patients receiving NUBEQA. Seizure occurred from 261 to 665 days after initiation of NUBEQA.

In ARASENS, seizure occurred in 0.8% of patients receiving NUBEQA with docetaxel, including two Grade 3 events. Seizure occurred from 38 to 1754 days after initiation of NUBEQA.

It is unknown whether anti-epileptic medications will prevent seizures with NUBEQA. Advise patients of the risk of developing a seizure while receiving NUBEQA and of engaging in any activity where sudden loss of consciousness could cause harm to themselves or others. Consider discontinuation of NUBEQA in patients who develop a seizure during treatment.

5.3 Embryo-Fetal Toxicity

The safety and efficacy of NUBEQA have not been established in females. Based on its mechanism of action, NUBEQA can cause fetal harm and loss of pregnancy when administered to a pregnant female [see Clinical Pharmacology (12.1)].

Advise males with female partners of reproductive potential to use effective contraception during treatment and for 1 week after the last dose of NUBEQA [see Use in Specific Populations (8.1, 8.3)].

6 ADVERSE REACTIONS

6.1 Clinical Trials Experience

Because clinical trials are conducted under widely varying conditions, adverse reaction rates observed in the clinical trials of a drug cannot be directly compared to rates in the clinical trials of another drug and may not reflect the rates observed in practice.

The pooled data in WARNINGS and PRECAUTIONS reflect two randomized clinical trials [ARAMIS, ARANOTE] in patients with nmCRPC (N = 954) and mCSPC (N = 445) treated with NUBEQA. In these trials, the median duration of treatment was 18.2 months (range 0.03 to 44.3) for patients who received NUBEQA [see Clinical Studies (14)]. In this pooled safety population, the most common adverse reactions (>10% with a ≥2% increase over placebo), including laboratory test abnormalities were increased AST, decreased neutrophil count, increased bilirubin, fatigue and increased ALT.

The safety of NUBEQA in combination with docetaxel in mCSPC is based on data from 1302 patients of whom 652 received at least one dose of NUBEQA in the ARASENS study [see Clinical Studies (14)].

Non-Metastatic Castration Resistant Prostate Cancer

ARAMIS

The safety of NUBEQA in nmCRPC patients was evaluated in ARAMIS, a randomized (2:1), double-blind, placebo-controlled, multi-center clinical study [see Clinical Studies (14)]. Patients received either NUBEQA at a dose of 600 mg, or a placebo, twice a day. All patients in the ARAMIS study received a concomitant gonadotropin-releasing hormone (GnRH) analog or had a bilateral orchiectomy. Among patients who received NUBEQA, the median duration of exposure was 14.8 months (range: 0 to 44.3 months).

Serious adverse reactions occurred in 25% of patients receiving NUBEQA and in 20% of patients receiving placebo. Serious adverse reactions in ≥1% of patients who received NUBEQA included urinary retention, pneumonia and hematuria. Fatal adverse reactions occurred in 3.9% of patients receiving NUBEQA and 3.2% of patients receiving placebo. Fatal adverse reactions that occurred in ≥2 patients who received NUBEQA included death (0.4%), cardiac failure (0.3%), cardiac arrest (0.2%), general physical health deterioration (0.2%), and pulmonary embolism (0.2%).

Permanent discontinuation of NUBEQA due to adverse reactions occurred in 9% of patients receiving NUBEQA. The most common adverse reactions requiring permanent discontinuation in patients who received NUBEQA included cardiac failure (0.4%), and death (0.4%).

Dosage interruptions due to adverse reactions occurred in 13% of patients treated with NUBEQA. The most common adverse reactions requiring dosage interruption in patients who received NUBEQA included hypertension (0.6%), diarrhea (0.5%), and pneumonia (0.5%).

Dosage reductions due to adverse reactions occurred in 6% of patients treated with NUBEQA. The most common adverse reactions requiring dosage reduction in patients treated with NUBEQA included fatigue (0.7%), hypertension (0.3%), and nausea (0.3%).

The most common (>2% with a ≥2% increase compared to placebo) adverse reactions, including laboratory test abnormalities, were increased AST, decreased neutrophil count, fatigue, increased bilirubin, pain in extremity, and rash.

Table 1 summarizes the adverse reactions in ARAMIS.

Table 1: Adverse Reactions (>2% with a ≥2% increase compared to placebo) in Patients with nmCRPC in ARAMIS
Adverse Reaction | NUBEQA (N=954) |  | Placebo (N=554)
Adverse Reaction | All Grades % | Grades 3 or 4 % | All Grades % | Grade 3 or 4 %
Fatigue [Includes fatigue and asthenia] | 16 | 0.6 | 11 | 1.1
Pain in extremity | 6 | 0 | 3 | 0.2
Rash [Includes rash, eczema, rash maculo-papular, dermatitis, erythema multiforme, rash macular, rash papular, rash pustular, skin exfoliation] | 4 | 0.1 | 1.4 | 0

Clinically relevant adverse reactions occurring in 2% or more of patients treated with NUBEQA included ischemic heart disease (4%) and heart failure (2.1%).

Table 2 summarizes the laboratory test abnormalities in ARAMIS.

Table 2: Laboratory Test Abnormalities in ARAMIS
Laboratory Abnormality | NUBEQA (N=954) [The denominator used to calculate the rate varied based on the number of patients with a baseline value and at least one post-treatment value.] |  | Placebo (N=554)
Laboratory Abnormality | All Grades % | Grade 3 or 4 % | All Grades % | Grade 3 or 4 %
AST increased | 23 | 0.5 | 14 | 0.2
Neutrophil count decreased | 20 | 4 | 9 | 0.6
Bilirubin increased | 16 | 0.1 | 7 | 0

Metastatic Castration-Sensitive Prostate Cancer

ARANOTE

The safety of NUBEQA in mCSPC patients was evaluated in ARANOTE, a randomized (2:1), double-blind, placebo-controlled, multi-center clinical study [see Clinical Studies (14)]. Patients received either NUBEQA at a dose of 600 mg, or a placebo, twice a day. All patients in the ARANOTE study received a concomitant gonadotropin-releasing hormone (GnRH) agonist or antagonist or had a bilateral orchiectomy. Among patients who received NUBEQA, the median duration of exposure was 24 months (range: 0.03 to 39 months).

Serious adverse reactions occurred in 24% of patients receiving NUBEQA. Serious adverse reactions in ≥1% of patients who received NUBEQA included pneumonia (2%), urinary tract infection (1.8%), musculoskeletal pain (1.6%), hemorrhage (1.6%), arrhythmias (1.3%), and spinal cord compression (1.1%). Fatal adverse reactions occurred in 4.7% of patients receiving NUBEQA and those that occurred in ≥2 patients included sepsis (1.1%), craniocerebral injury (0.4%), and myocardial infarction (0.4%).

Permanent discontinuation of NUBEQA due to adverse reactions occurred in 6% of patients treated in the NUBEQA arm. The most common adverse reactions which resulted in permanent discontinuation of NUBEQA were increased ALT, increased AST, craniocerebral injury, myocardial infarction, and rash (all with 0.4%).

Dosage interruptions of NUBEQA due to adverse reactions occurred in 14% of patients treated in the NUBEQA arm. The most common adverse reactions requiring dosage interruption of NUBEQA were increased AST (1.6%), increased ALT (1.3%), and rash (1.3%).

Dosage reductions of NUBEQA due to adverse reactions occurred in 3.6% of patients treated in the NUBEQA arm. The most common adverse reactions requiring dosage reduction of NUBEQA were increased AST (0.7%), rash (0.7%), increased ALT (0.4%), and hypertension (0.4%).

Table 3 summarizes the adverse reactions in ARANOTE.

Table 3: Adverse Reactions (≥10% with a ≥2% increase compared to placebo) in Patients with mCSPC in ARANOTE
Adverse Reaction | NUBEQA (N=445) |  | Placebo (N=221)
Adverse Reaction | All Grades (%) | Grade 3 or 4 (%) | All Grades (%) | Grade 3 or 4 (%)
Urinary Tract Infection | 12 | 1.8 | 8 | 0.5

Clinically relevant adverse reactions in <10% of patients who received NUBEQA included arrhythmia (8.8%), pneumonia (3.6%), and myocardial infarction (0.7%).

Table 4 summarizes the laboratory test abnormalities in ARANOTE.

Table 4: Laboratory Test Abnormalities (≥15% with a ≥5% increase over placebo) in ARANOTE
Laboratory Abnormality | NUBEQA (N=445) [The number of patients tested for a specific laboratory test parameter may be different. The incidence of each laboratory test abnormality was calculated accordingly.] |  | Placebo (N=221)
Laboratory Abnormality | All Grades [Common Terminology Criteria for Adverse Events (CTCAE) version 5.0. Grade 4 laboratory test values were limited to neutrophil count decreased.] % | Grade 3 or 4 % | All Grades % | Grade 3 or 4 %
AST increased | 32 | 2.8 | 25 | 0.5
ALT increased | 28 | 2.1 | 23 | 0.5
Bilirubin increased | 17 | 0.5 | 7 | 0
Neutrophil count decreased | 16 | 1.2 | 9 | 0.5

ARASENS

The safety of NUBEQA, in combination with docetaxel, in mCSPC patients was evaluated in ARASENS, a randomized (1:1), double-blind, placebo-controlled, multi-center clinical study [see Clinical Studies (14)]. Patients were to receive either NUBEQA at a dose of 600 mg, or a placebo, twice a day in combination with docetaxel at a dose of 75 mg/m2 every 21 days for 6 cycles. All patients in the ARASENS study received a concomitant gonadotropin-releasing hormone (GnRH) agonist or antagonist or had a bilateral orchiectomy. Among patients who received NUBEQA, the median duration of exposure was 41 months (range: 0.1 to 56.5 months) vs. 16.7 months (range 0.3 to 55.8) with placebo. Eighty-eight percent and 86% of patients received the 6 planned cycles of docetaxel, in the NUBEQA with docetaxel arm and placebo with docetaxel arm, respectively.

Serious adverse reactions occurred in 45% of patients receiving NUBEQA with docetaxel. Serious adverse reactions in ≥ 2% of patients who received NUBEQA with docetaxel included febrile neutropenia (6%), neutrophil count decreased (2.8%), musculoskeletal pain (2.6%) and pneumonia (2.6%). Fatal adverse reactions occurred in 4% of patients receiving NUBEQA with docetaxel. Fatal adverse reactions in ≥2 patients who received NUBEQA included COVID-19/COVID-19 pneumonia (0.8%), myocardial infarction (0.3%), and sudden death (0.3%).

Permanent discontinuation of NUBEQA due to adverse reactions occurred in 14% of patients treated in the NUBEQA with docetaxel arm. The most common adverse reactions which resulted in permanent discontinuation of NUBEQA were rash (1.1%), musculoskeletal pain (0.9%), and increased aspartate aminotransferase (AST) (0.9%).

Dosage interruptions of NUBEQA due to adverse reactions occurred in 23% of patients treated in the NUBEQA with docetaxel arm. The most common (>2%) adverse reactions requiring dosage interruption of NUBEQA were increased alanine aminotransferase (ALT) (3.2%), increased AST (3.1%) and febrile neutropenia (2.1%).

Dosage reductions of NUBEQA due to adverse reactions occurred in 9% of patients treated in the NUBEQA with docetaxel arm. The most common (>2%) adverse reactions requiring dosage reduction of NUBEQA were increased ALT (2.8%) and increased AST (2.5%).

The most common (>10% with a ≥2% increase over placebo with docetaxel) adverse reactions are constipation, rash, decreased appetite, hemorrhage, increased weight, and hypertension. The most common laboratory test abnormalities (≥30%) are anemia, hyperglycemia, decreased lymphocyte count, decreased neutrophil count, increased AST, increased ALT, and hypocalcemia.

Table 5 summarizes the adverse reactions in ARASENS.

Table 5: Adverse Reactions (≥10% with a ≥2% increase compared to placebo with docetaxel) in ARASENS
Adverse Reaction | NUBEQA with docetaxel (N=652) |  | Placebo with docetaxel (N=650)
Adverse Reaction | All Grades % | Grades 3 or 4 % | All Grades % | Grades 3 or 4 %
Constipation | 23 | 0.3 | 20 | 0.3
Rash [Rash includes rash, rash maculo-papular, palmar-plantar erythrodysesthesia syndrome, eczema, dermatitis, skin exfoliation, dermatitis acneiform, drug eruption, rash pruritic, rash erythematous, erythema multiforme, rash macular, dermatitis exfoliative generalized, penile rash, dyshidrotic eczema, rash papular, dermatitis bullous, rash follicular, rash pustular, rash vesicular, toxic skin eruption] | 20 | 1.8 | 15 | 0.2
Decreased Appetite | 19 | 0.2 | 13 | 0.6
Hemorrhage [Hemorrhage includes hematuria, epistaxis, anal hemorrhage, hemorrhoidal hemorrhage, rectal hemorrhage, upper gastrointestinal hemorrhage, hemoptysis, hemorrhage urinary tract, hemorrhagic stroke, subarachnoid hemorrhage, lower gastrointestinal hemorrhage, cystitis hemorrhagic, gastrointestinal hemorrhage, hemorrhage subcutaneous, intra-abdominal hemorrhage, nail bed bleeding, subdural hemorrhage] | 18 | 1.4 | 13 | 1.4
Weight Increased | 18 | 2.1 | 16 | 1.2
Hypertension [Hypertension includes hypertension, blood pressure increased, hypertensive emergency and hypertensive crisis.] | 14 | 7 | 10 | 3.6

Clinically relevant adverse reactions in < 10% of patients who received NUBEQA with docetaxel included fractures (8%), ischemic heart disease (3.2%), seizures (0.6%), and drug-induced liver injury (0.3%).

Table 6 summarizes laboratory test abnormalities in the ARASENS study.

Table 6: Laboratory Test Abnormalities (≥30%) in ARASENS
Laboratory Abnormality | NUBEQA with docetaxel [The denominator used to calculate the rate varied from 470 to 648 based on the number of patients with a baseline value and at least one post-treatment value.] (N=652) |  | Placebo with docetaxel (N=650)
Laboratory Abnormality | All Grades % | Grade 3-4 % | All Grades % | Grade 3-4 %
Anemia | 72 | 6 | 71 | 7
Hyperglycemia | 57 | 7 | 53 | 10
Lymphocyte count decreased | 52 | 12 | 49 | 13
Neutrophil count decreased | 49 | 33 | 44 | 31
AST increased [ALT or AST increases to ≥5 × upper limit of normal (ULN) occurred in 5.3% of patients who received NUBEQA with docetaxel. ALT or AST increases to ≥20 × ULN occurred in 0.3% of patients who received NUBEQA with docetaxel. The median time to onset of any grade ALT or AST increases was 2.8 months (range: 0.03 to 46.9).] | 40 | 3.6 | 35 | 2.3
ALT increased | 37 | 3.7 | 31 | 2.9
Hypocalcemia | 31 | 2.8 | 28 | 1.9

Clinically relevant laboratory test abnormalities in < 30% of patients who received NUBEQA with docetaxel included blood bilirubin increased (all grades 20%, Grade 3-4 0.5%) compared to placebo with docetaxel (all grades 10%, grades 3-4 0.3%).

7 DRUG INTERACTIONS

7.1 Effects of Other Drugs on NUBEQA

Combined P-gp and Strong or Moderate CYP3A4 Inducer

Concomitant use of NUBEQA with a combined P-gp and strong or moderate CYP3A4 inducer decreases darolutamide exposure which may decrease NUBEQA activity [see Clinical Pharmacology (12.3)]. Avoid concomitant use of NUBEQA with combined P-gp and strong or moderate CYP3A4 inducers.

Combined P-gp and Strong CYP3A4 Inhibitors

Concomitant use of NUBEQA with a combined P-gp and strong CYP3A4 inhibitor increases darolutamide exposure [see Clinical Pharmacology (12.3)] which may increase the risk of NUBEQA adverse reactions. Monitor patients more frequently for NUBEQA adverse reactions and modify NUBEQA dosage as needed [see Dosage and Administration (2.2)].

7.2 Effects of NUBEQA on Other Drugs

Breast Cancer Resistance Protein (BCRP) and Organic Anion Transporting Polypeptides (OATP) 1B1 and 1B3 Substrates

NUBEQA is an inhibitor of BCRP transporter. Concomitant use of NUBEQA increases the AUC and Cmax of BCRP substrates [see Clinical Pharmacology (12.3)], which may increase the risk of BCRP substrate-related toxicities.

Avoid concomitant use with drugs that are BCRP substrates where possible. If used together, monitor patients more frequently for adverse reactions, and consider dose reduction of the BCRP substrate drug.

NUBEQA is an inhibitor of OATP1B1 and OATP1B3 transporters. Concomitant use of NUBEQA may increase the plasma concentrations of OATP1B1 or OATP1B3 substrates. Monitor patients more frequently for adverse reactions of these drugs and consider dose reduction while patients are taking NUBEQA [see Clinical Pharmacology (12.3)],

Review the prescribing information of the BCRP, OATP1B1 and OATP1B3 substrates when used concomitantly with NUBEQA.

8 USE IN SPECIFIC POPULATIONS

8.1 Pregnancy

Risk Summary

The safety and efficacy of NUBEQA have not been established in females. Based on its mechanism of action, NUBEQA can cause fetal harm and loss of pregnancy [see Clinical Pharmacology (12.1)]. Animal embryo-fetal developmental toxicology studies were not conducted with darolutamide. There are no human data on the use of NUBEQA in pregnant females.

8.2 Lactation

Risk Summary

The safety and efficacy of NUBEQA have not been established in females. There are no data on the presence of darolutamide or its metabolites in human milk, the effect on the breastfed child, or the effect on milk production.

8.3 Females and Males of Reproductive Potential

Contraception

Males

Based on the mechanism of action, advise male patients with female partners of reproductive potential to use effective contraception during treatment and for 1 week after the last dose of NUBEQA [see Use in Specific Populations (8.1)].

Infertility

Males

Based on animal studies, NUBEQA may impair fertility in males of reproductive potential [see Nonclinical Toxicology (13.1)].

8.4 Pediatric Use

Safety and effectiveness of NUBEQA in pediatric patients have not been established.

8.5 Geriatric Use

Of the 954 patients who received NUBEQA in ARAMIS, 88% of patients were 65 years and over, and 49% were 75 years and over. Of the 445 patients who received NUBEQA in ARANOTE, 74% of patients were 65 years and over, and 30% were 75 years and over. Of the 652 patients who received NUBEQA in ARASENS, 63% of patients were 65 years and over, and 16% were 75 years and over. No overall differences in safety or efficacy were observed between these patients and younger patients in both studies.

8.6 Renal Impairment

Patients with severe renal impairment (eGFR 15–29 mL/min/1.73 m^2) who are not receiving hemodialysis have a higher exposure to NUBEQA and reduction of the dose is recommended [see Dosage and Administration (2.3) and Clinical Pharmacology (12.3)]. No dose reduction is needed for patients with mild or moderate renal impairment (eGFR 30-89 mL/min/1.73 m^2). The effect of end stage renal disease (eGFR ≤15 mL/min/1.73 m^2) on darolutamide pharmacokinetics is unknown.

8.7 Hepatic Impairment

Patients with moderate hepatic impairment (Child-Pugh Class B) have a higher exposure to NUBEQA and reduction of the dose is recommended [see Dosage and Administration (2.4) and Clinical Pharmacology (12.3)]. No dose reduction is needed for patients with mild hepatic impairment. The effect of severe hepatic impairment (Child-Pugh C) on darolutamide pharmacokinetics is unknown.

10 OVERDOSAGE

There is no known specific antidote for darolutamide overdose. The highest dose of NUBEQA studied clinically was 900 mg twice daily, equivalent to a total daily dose of 1800 mg. No dose limiting toxicities were observed with this dose.

Considering the saturable absorption and the absence of evidence for acute toxicity, an intake of a higher than recommended dose of darolutamide is not expected to lead to systemic toxicity in patients with intact hepatic and renal function [see Clinical Pharmacology (12.3)].

In the event of intake of a higher than recommended dose in patients with severe renal impairment or moderate hepatic impairment, if there is suspicion of toxicity, interrupt NUBEQA treatment and undertake general supportive measures until clinical toxicity has been diminished or resolved. If there is no suspicion of toxicity, NUBEQA treatment can be continued with the next dose as scheduled.

11 DESCRIPTION

NUBEQA is an androgen receptor inhibitor. The chemical name is N-{(2S)-1-[3-(3-chloro-4-cyanophenyl)-1H-pyrazol-1-yl]propan-2-yl}-5-(1-hydroxyethyl)-1H-pyrazole-3-carboxamide.

The molecular weight is 398.85 and the molecular formula is C19H19Cl N6O2. The structural formula is:

Darolutamide is an optically active with a specific rotation value [α]^20D= 72.2 o*mL/(dm*g), white to greyish- or yellowish white crystalline powder, that is soluble in tetrahydrofuran, but practically insoluble in aqueous medium. Darolutamide has a pKa of 11.75.

NUBEQA (darolutamide) is supplied as film-coated tablets containing 300 mg of darolutamide for oral use. The inactive ingredients of the tablet are: calcium hydrogen phosphate, croscarmellose sodium, lactose monohydrate, magnesium stearate, povidone K 30, hypromellose 15 cP, macrogol 3350, and titanium dioxide.

12 CLINICAL PHARMACOLOGY

12.1 Mechanism of Action

Darolutamide is an androgen receptor (AR) inhibitor. Darolutamide competitively inhibits androgen binding, AR nuclear translocation, and AR-mediated transcription. A major metabolite, ketodarolutamide, exhibited similar in vitro activity to darolutamide. In addition, darolutamide functioned as a progesterone receptor (PR) antagonist in vitro (approximately 1% activity compared to AR). Darolutamide decreased prostate cancer cell proliferation in vitro and tumor volume in mouse xenograft models of prostate cancer.

12.2 Pharmacodynamics

PSA reduction was observed in CRPC patients receiving darolutamide doses of 100-900 mg twice a day, reaching a plateau of PSA reduction at the 600 mg twice daily dose.

Twice daily dosing of 600 mg darolutamide in nmCRPC patients resulted in undetectable PSA levels in 24% of patients at 12 months compared to 0.4% of patients in the placebo arm.

Twice daily dosing of 600 mg darolutamide in mCSPC patients resulted in undetectable PSA levels (<0.2 ng/mL) in 63% of patients compared to 19% of patients in the placebo arm.

Twice daily dosing of 600 mg darolutamide in combination with docetaxel in mCSPC patients resulted in undetectable PSA levels in 60% of patients at 12 months compared to 26% of patients in the placebo with docetaxel arm.

Cardiac Electrophysiology

The effect of darolutamide (600 mg twice daily) on the QTc interval was evaluated in a subgroup of 500 patients in the ARAMIS study. No large mean increase in QTc (i.e., > 20 ms) was detected.

12.3 Pharmacokinetics

Following administration of 600 mg twice daily, darolutamide mean (%CV) steady-state peak plasma concentration (Cmax) is 4.79 mg/L (30.9%) and area under the plasma concentration-time curve from time 0 to 12 hours (AUC12h) is 52.82 h∙µg/mL (33.9%). Steady-state is reached 2–5 days after repeated dosing with food, with an approximate 2-fold accumulation.

The exposure (Cmax and AUC12) of the darolutamide and the active metabolite ketodarolutamide increase in a nearly dose-proportional manner in the dose range of 100 to 700 mg (0.17 to 1.17 times the approved recommended dosage). No further increase in darolutamide exposure was observed at 900 mg twice daily (1.5 times the approved recommended dosage).

Absorption

Darolutamide Cmax is reached approximately 4 hours after administration of a single 600 mg oral dose.

The absolute bioavailability is approximately 30% following oral administration of a NUBEQA tablet containing 300 mg darolutamide under fasted conditions.

Food Effect

Bioavailability of darolutamide increased by 2.0- to 2.5‑fold when administered with food. A similar increase of exposure was observed for the active metabolite ketodarolutamide.

Distribution

The apparent volume of distribution of darolutamide after intravenous administration is 119 L.

Protein binding is 92% for darolutamide and 99.8% for the active metabolite, ketodarolutamide. Serum albumin is the main binding protein for darolutamide and ketodarolutamide.

Elimination

The effective half-life of darolutamide and ketodarolutamide is approximately 20 hours in patients. The clearance (%CV) of darolutamide following intravenous administration is 116 mL/min (39.7%).

Metabolism

Darolutamide is primarily metabolized by CYP3A4, as well as by UGT1A9 and UGT1A1. Ketodarolutamide total exposure in plasma is 1.7‑fold higher compared to darolutamide.

Excretion

After a single radiolabeled dose as an oral solution, a total of 63.4% of darolutamide‑related material is excreted in the urine (approximately 7% unchanged) and 32.4% (approximately 30% unchanged) in the feces. More than 95% of the dose was recovered within 7 days after administration.

Specific Populations

No clinically significant differences in the pharmacokinetics of darolutamide were observed based on age (41-95 years), race (White, Asian, Black or African American), mild to moderate renal impairment (eGFR 30–89 mL/min/1.73m^2), or mild hepatic impairment.

In non-cancer subjects with severe renal impairment (eGFR 15–29 mL/min/1.73 m^2) not receiving dialysis or with moderate hepatic impairment (Child-Pugh Class B), NUBEQA exposure increased by about 2.5- and 1.9-fold, respectively, compared to healthy subjects.

The effect of end-stage renal disease (eGFR <15 mL/min/1.73 m^2) or severe hepatic impairment (Child-Pugh C) on darolutamide pharmacokinetics has not been studied.

Drug Interaction Studies

Clinical Studies

Combined P-gp and Strong CYP3A4 Inducers

Concomitant use of rifampicin (a combined P-gp and strong CYP3A4 inducer) decreased mean darolutamide AUC0-72 by 72% and Cmax by 52%. The decrease of darolutamide exposure by moderate CYP3A4 inducers is expected to be in the range of 36% – 58%.

Combined P-gp and Strong CYP3A4 Inhibitors

Itraconazole (a strong combined CYP3A4 and P-gp inhibitor) increased mean darolutamide AUC0-72 by 1.7- and Cmax by 1.4-fold.

CYP3A4 substrates

Concomitant use of darolutamide decreased the mean AUC and Cmax of midazolam (CYP3A4 substrate) by 29% and 32%, respectively. No clinically relevant differences in the pharmacokinetics of midazolam were observed when used concomitantly with darolutamide.

BCRP, OATP1B1 and OATP1B3 Substrates

Concomitant use of darolutamide increased the mean AUC and Cmax of rosuvastatin (BCRP, OATP1B1 and OATP1B3 substrate) by approximately 5-fold.

Docetaxel

Administration of darolutamide in combination with docetaxel resulted in no clinically relevant changes in the pharmacokinetics of docetaxel in mCSPC patients. There were no clinically relevant changes in the pharmacokinetics of darolutamide, when used in combination with docetaxel.

P-gp Substrates

No clinically relevant differences in the pharmacokinetics of dabigatran (P-gp substrate) were observed when used concomitantly with darolutamide.

In vitro, darolutamide did not inhibit the major CYP enzymes (CYP1A2, 2A6, 2B6, 2C8, 2C9, 2C19, 2D6, 2E1, and 3A4) or transporters (MRP2, BSEP, OATs, OCTs, MATEs, OATP2B1, and NTCP) at clinically relevant concentrations.

13 NONCLINICAL TOXICOLOGY

13.1 Carcinogenesis, Mutagenesis, Impairment of Fertility

Oral administration of darolutamide to male and female RasH2 transgenic mice for 26 weeks did not show carcinogenic potential at doses up to 1000 mg/kg/day.

Darolutamide was clastogenic in an in vitro chromosome aberration assay in human peripheral blood lymphocytes. Darolutamide did not induce mutations in the bacterial reverse mutation (Ames) assay and was not genotoxic in the in vivo combined bone marrow micronucleus assay and the Comet assay in the liver and duodenum of the rat.

Fertility studies in animals have not been conducted with darolutamide. In repeat-dose toxicity studies in male rats (up to 26 weeks) and dogs (up to 39 weeks), tubular dilatation of testes, hypospermia, and atrophy of seminal vesicles, testes, prostate gland and epididymides were observed at doses ≥ 100 mg/kg/day in rats (0.6 times the human exposure based on AUC) and ≥ 50 mg/kg/day in dogs (approximately 1 times the human exposure based on AUC).

14 CLINICAL STUDIES

Non-Metastatic Castration Resistant Prostate Cancer

ARAMIS (NCT02200614) was a multicenter, double-blind, placebo-controlled clinical trial in 1509 patients with non-metastatic castration resistant prostate cancer with a prostate-specific antigen doubling time (PSADT) of ≤ 10 months. Randomization was stratified by PSADT and use of bone-targeted therapy at study entry. Patients with pelvic lymph nodes less than 2 cm in short axis below the aortic bifurcation were eligible to enter the study. Absence or presence of metastasis was assessed by blinded independent central review (BICR). PSA results were not blinded and were not used for treatment discontinuation.

Patients were randomized 2:1 to receive either 600 mg NUBEQA orally twice daily (n=955) or matching placebo (n=554). Treatment continued until radiographic disease progression as assessed by CT, MRI, 99mTc bone scan by BICR, unacceptable toxicity or withdrawal. All patients received a gonadotropin-releasing hormone (GnRH) analog concurrently or had a bilateral orchiectomy.

The median age was 74 years (range 48–95) and 9% of patients were 85 years of age or older. The racial distribution included 79% White, 13% Asian, 3% Black or African American, while ethnicity included 3.1% Hispanic or Latino patients. A majority of patients (73%) had a Gleason score of 7 or higher at diagnosis. The median PSADT was 4.5 months. Forty-two percent of patients in both treatment arms had prior surgery or radiotherapy to the prostate. Eleven percent of patients had enlarged pelvic lymph nodes less than 2 cm at study entry. Six percent of patients were retrospectively identified by BICR as having metastases at baseline. Seventy-three percent of patients received prior treatment with an anti-androgen (bicalutamide or flutamide). All patients had an Eastern Cooperative Oncology Group Performance Status (ECOG PS) score of 0 or 1 at study entry. At baseline, 47% of patients reported no pain on the Brief Pain Inventory-Short Form (a 7-day diary average of the daily worst pain item). There were 12 patients (1.3%) enrolled on the NUBEQA arm with a history of seizure.

The major efficacy endpoint was metastasis free survival (MFS), defined as the time from randomization to the time of first evidence of BICR-confirmed distant metastasis or death from any cause within 33 weeks after the last evaluable scan, whichever occurred first. Distant metastasis was defined as new bone or soft tissue lesions or enlarged lymph nodes above the aortic bifurcation. Overall survival (OS), time to pain progression, and time to initiation of cytotoxic chemotherapy, were additional efficacy endpoints.

Treatment with NUBEQA resulted in a statistically significant improvement in MFS compared to placebo. At the protocol-specified final analysis of OS, treatment with NUBEQA resulted in a statistically significant improvement in OS compared to placebo. The final analysis of OS and time to initiation of cytotoxic chemotherapy was event-driven and conducted after 254 OS events had occurred. The efficacy results from ARAMIS are summarized in Table 7 and Figure 1.

Table 7: Efficacy Results from the ARAMIS Study
 | NUBEQA (N=955) | Placebo (N=554)
Metastasis-free survival [Locoregional-only progression occurred in 6% of patients overall.]
Distant Metastasis or Death (%) | 221 (23) | 216 (39)
Median, months (95% CI) [Based on Kaplan-Meier estimates] | 40.4 (34.3, NR) | 18.4 (15.5, 22.3)
Hazard Ratio (95% CI) [Hazard ratio is based on a stratified Cox regression model. Hazard ratio < 1 favors NUBEQA.] | 0.41 (0.34, 0.50)
P-value [The pre-specified final OS analysis was event-driven and occurred 14 months after the MFS analysis] | <0.0001
Overall survival
Deaths (%) | 148 (15) | 106 (19)
Median, months (95% CI) | NR (56.1, NR) | NR (46.9, NR)
Hazard Ratio (95% CI) | 0.69 (0.53, 0.88)
P-value [P-value is based on a log-rank test stratified by PSADT (≤ 6 months vs. > 6 months) and use of osteoclast-targeted therapy (yes vs. no)] | 0.003
NR: not reached

Figure 1: Kaplan-Meier Curve Metastasis Free Survival; Intent-To-Treat nmCRPC population (ARAMIS)

Figure 2: Kaplan-Meier curves of Overall Survival; Intent-To-Treat nmCRPC population (ARAMIS)

MFS results were consistent across patient subgroups for PSADT (≤ 6 months or > 6 months) or prior use of bone-targeting agents (yes or no).

Treatment with NUBEQA resulted in a statistically significant delay in time to pain progression (HR = 0.65, 95% CI= 0.53, 0.79; p < 0.0001). Time to pain progression was defined as at least a 2-point worsening from baseline of the pain score on Brief Pain Inventory Short Form or initiation of opioids and reported in 28% of all patients on study.

Treatment with NUBEQA resulted in a statistically significant delay in the initiation of cytotoxic chemotherapy (HR = 0.58, 95% CI = 0.44, 0.76; p < 0.0001).

Metastatic Castration Sensitive Prostate Cancer (mCSPC)

ARANOTE

ARANOTE (NCT02799602) was a multicenter, double-blind, placebo-controlled study in 669 patients with mCSPC. Patients were randomized 2:1 to receive 600 mg NUBEQA orally twice daily (n=446) or matching placebo (n=223). Patients with both high- and low-volume mCSPC were eligible for the study. High-volume disease was defined as presence of visceral metastases, or 4 or more bone lesions, with at least 1 metastasis beyond the vertebral column and pelvic bones. Randomization was stratified by presence of visceral metastasis and use of prior local therapy at study entry. All patients received a gonadotropin-releasing hormone (GnRH) agonist or antagonist concurrently or had a bilateral orchiectomy. Treatment with NUBEQA or placebo continued until progressive disease, change of antineoplastic therapy, unacceptable toxicity, death, or withdrawal.

The median age was 70 years (range 43-93) and 29% of patients were 75 years of age or older. The racial distribution was 56% White, 31% Asian, and 10% Black; while ethnicity included 24% Hispanic patients. Sixty-eight percent (68%) of patients had a Gleason score of 8 or higher at diagnosis. At study entry, ECOG PS of 0, 1, and 2 were 50%, 47%, and 3%, respectively. Seventy-three percent (73%) of patients had de novo disease and 22% had recurrent disease. Seventy-one percent (71%) of patients had high-volume disease, including 12% with visceral metastases, and 29% had low-volume disease. The median PSA level at baseline was 21 µg/L. One patient (0.2%) with a medical history of seizure was treated with NUBEQA in ARANOTE.

The major efficacy outcome measure was radiographic progression-free survival (rPFS), defined as the time from randomization to radiological disease progression or death by central blinded review. Radiographic disease progression was defined by identification of 2 or more new bone lesions on a bone scan with confirmation (Prostate Cancer Working Group 3 criteria) and/or progression in soft tissue disease. Additional efficacy outcome measure was overall survival (OS).

Treatment with NUBEQA resulted in a statistically significant improvement in rPFS compared to placebo. There was no statistically significant improvement in OS.

Efficacy results for ARANOTE are shown in Table 8 and Figure 3.

Table 8: Efficacy Results in Patients with mCSPC in ARANOTE
Efficacy Endpoint | NUBEQA (N=446) | Placebo (N=223)
Radiographic Progression-Free Survival
Patients with event, n (%) | 128 (29) | 94 (42)
Median, months (95% CI) | NR (NR, NR) | 25 (19, NR)
Hazard ratio (95% CI) [Based on stratified Cox regression model] | 0.54 (0.41, 0.71)
p-value [Based on stratified log-rank test] | <0.0001
Overall Survival
Patients with event, n (%) | 115 (26) | 70 (31)
Median, months (95% CI) | NR (NR, NR) | NR (NR, NR)
Hazard Ratio (95% CI) | 0.78 (0.58, 1.05)
p-value | NS
NR: not reached
NS: not statistically significant

Figure 3: Kaplan-Meier Curves for Radiographic Progression-Free Survival; mCSPC population (ARANOTE)

ARASENS

ARASENS (NCT02799602) was a multicenter, double-blind, placebo-controlled clinical trial in 1306 patients with mCSPC. Patients were randomized 1:1 to receive 600 mg NUBEQA orally twice daily (n=651) or matching placebo (n=655), concomitantly with 75 mg/m^2 of docetaxel for 6 cycles. All patients received a gonadotropin-releasing hormone (GnRH) agonist or antagonist concurrently or had a bilateral orchiectomy. Treatment with NUBEQA or placebo continued until symptomatic progressive disease, change of antineoplastic therapy, or unacceptable toxicity. Patients with regional lymph node involvement only (M0) were excluded from the study. Patients were stratified by extent of disease (non–regional lymph nodes metastases only (M1a), bone metastases with or without lymph node metastases (M1b) or visceral metastases with or without lymph node metastases or with or without bone metastases (M1c)) and by alkaline phosphatase level (< or ≥ upper limit of normal) at study entry.

The median age was 67 years (range 41–89) and 17% of patients were 75 years of age or older. The racial distribution included 52% White, 36% Asian, 4% Black, while ethnicity included 7% Hispanic patients. Seventy-eight percent (78%) of patients had a Gleason score of ≥8 at diagnosis. Seventy one percent (71%) of patients had an ECOG performance status score of 0 and 29% patients had an ECOG performance status score of 1. There were 86% of patients with de novo and 13% with recurrent disease. At initial diagnosis of metastatic disease, 3% had M1a, 83% had M1b and 14% had M1c disease; alkaline phosphatase was < ULN in 45% of patients and ≥ ULN in 55% of patients; median PSA level at baseline was 30 µg/L and 24 µg/L for NUBEQA vs placebo group, respectively. Four patients (0.6%) with a medical history of seizure were treated with NUBEQA with docetaxel in ARASENS.

The major efficacy outcome measure was overall survival (OS). Time to pain progression was an additional efficacy outcome measure.

Treatment with NUBEQA with docetaxel resulted in a statistically significant improvement in OS compared to placebo with docetaxel. OS results were consistent across stratified subgroups (extent of disease and alkaline phosphatase level).

Efficacy results are shown in Table 9 and Figure 4.

Table 9: Efficacy Results from the ARASENS study
 | NUBEQA with docetaxel (N=651) | Placebo with docetaxel (N=654) [One patient in the placebo arm was excluded from all analyses due to the violation of Good Clinical Practices]
Overall survival
Deaths (%) | 229 (35) | 304 (46)
Median in months (95% CI) | NR (NR, NR) | 48.9 (44.4, NR)
Hazard Ratio (95% CI) [Hazard ratio < 1 favors NUBEQA] | 0.68 (0.57, 0.80)
P-value [P-value is one-sided, and based on a log-rank test stratified by extent of disease (non-regional lymph nodes metastases only or bone metastases with or without lymph node metastases or visceral metastases with or without lymph node metastases or with or without bone metastases) and Alkaline Phosphatase (ALP < ULN or ALP ≥ ULN)] | <0.0001
NR: not reached

Figure 4: Kaplan-Meier curves of Overall Survival; mCSPC population (ARASENS)

Treatment with NUBEQA with docetaxel resulted in a statistically significant delay in time to pain progression (HR = 0.79, 95% CI= 0.66, 0.95; 1-sided p value = 0.006). Time to pain progression was defined as the time from randomization to the time of pain progression. Pain progression is defined as:

- An increase of 2 or more points in the "worst pain in 24 hours" score (WPS) from nadir observed at 2 consecutive evaluations at least 4 weeks apart, or initiation of short- or long-acting opioid use for pain for at least 7 consecutive days, for asymptomatic patients (WPS=0) at baseline
- An increase of 2 or more points in the "worst pain in 24 hours" score (WPS) from nadir observed at 2 consecutive evaluations at least 4 weeks apart, and a WPS of 4 or greater, or initiation of short- or long-acting opioid use for pain for at least 7 consecutive days, for symptomatic patients (WPS ≥ 1) at baseline

Patients with opioid use within 4 weeks before randomization were censored at randomization in this analysis (125 patients (19%) in the NUBEQA with docetaxel arm and 118 patients (18%) in the placebo with docetaxel arm).

16 HOW SUPPLIED/STORAGE AND HANDLING

How Supplied

NUBEQA (darolutamide) 300 mg film-coated tablets are white to off-white, oval shaped tablets, marked with "300" on one side, and "BAYER" on the other side. NUBEQA 300 mg tablets are available in bottles of 120 tablets.

NDC 50419-395-01

Storage and Handling

Store at 20°C to 25°C (68°F to 77°F); excursions permitted between 15°C and 30°C (59°F and 86°F) [see USP Controlled Room Temperature].

Keep the bottle tightly closed after first opening.

17 PATIENT COUNSELING INFORMATION

Advise the patient to read the FDA-approved patient labeling (Patient Information)

Ischemic Heart Disease

Inform patients that NUBEQA has been associated with an increased risk of ischemic heart disease. Advise patients to seek immediate medical attention if any symptoms suggestive of an ischemic heart disease event occur [see Warnings and Precautions (5.1)].

Seizure

Inform patients that NUBEQA has been associated with an increased risk of seizure. Discuss conditions that may predispose to seizures and medications that may lower the seizure threshold. Advise patients of the risk of engaging in any activity where sudden loss of consciousness could cause serious harm to themselves or others. Inform patients to contact their healthcare provider right away if they have loss of consciousness or seizure [see Warnings and Precautions (5.2)].

Embryo-Fetal Toxicity

Inform patients that NUBEQA can be harmful to a developing fetus and can cause loss of pregnancy [see Use in Specific Populations (8.1)].

Advise male patients with female partners of reproductive potential to use effective contraception during treatment and for 1 week after the last dose of NUBEQA [see Warnings and Precautions (5.3) and Use in Specific Populations (8.1, 8.3)].

Dosage and Administration

Inform patients receiving concomitant gonadotropin-releasing hormone (GnRH) agonist or antagonist therapy that they need to maintain this treatment during the course of treatment with NUBEQA.

Instruct patients to take their dose of two tablets (twice daily). NUBEQA should be taken with food. Each tablet should be swallowed whole.

Inform patients that in the event of a missed daily dose of NUBEQA, to take any missed dose, as soon as they remember prior to the next scheduled dose, and not to take two doses together to make up for a missed dose [see Dosage and Administration (2.1)].

Infertility

Advise male patients that NUBEQA may impair fertility [see Use in Specific Populations (8.3)].

Manufactured by: Orion Corporation, Orion Pharma, FI-02101 Espoo, Finland
Manufactured for: Bayer HealthCare Pharmaceuticals Inc., Whippany, NJ 07981 USA

© 2019 Bayer HealthCare Pharmaceuticals Inc.

For more information, call Bayer HealthCare Pharmaceuticals Inc. at Bayer at 1-888-842-2937 or go to www.NUBEQA-us.com

PATIENT INFORMATION
NUBEQA® (NOO-bə-kə)
(darolutamide)
tablets

What is NUBEQA?
NUBEQA is a prescription medicine used to treat adults with prostate cancer:

- that has not spread to other parts of the body and no longer responds to a medical or surgical treatment that lowers testosterone
- that has spread to other parts of the body and responds to a medical or surgical treatment that lowers testosterone
- that has spread to other parts of the body and responds to a medical or surgical treatment that lowers testosterone in combination with docetaxel.

It is not known if NUBEQA is safe and effective in females or children.

Before taking NUBEQA, tell your healthcare provider about all your medical conditions, including if you:

- have heart problems
- have high blood pressure
- have diabetes
- have high amounts of fat or cholesterol in your blood (dyslipidemia)
- have a history of seizures, brain injury, stroke, or brain tumors
- have kidney or liver problems
- are pregnant or plan to become pregnant. NUBEQA can cause harm to your unborn baby and loss of pregnancy (miscarriage).
- have a partner who may become pregnant. Males who have female partners who may become pregnant should use effective birth control (contraception) during treatment and for 1 week after the last dose of NUBEQA. Talk with your healthcare provider about birth control methods.
- are breastfeeding or plan to breastfeed. It is not known if NUBEQA passes into breast milk.

Tell your healthcare provider about all the medicines you take, including prescription and over-the-counter medicines, vitamins, and herbal supplements. NUBEQA may affect the way other medicines work and other medicines may affect how NUBEQA works.
You should not start or stop any medicine before you talk with the healthcare provider that prescribed NUBEQA.
Know the medicines you take. Keep a list of them with you to show to your healthcare provider and pharmacist when you get a new medicine.

How should I take NUBEQA?

- Take NUBEQA exactly as your healthcare provider tells you.
- Your healthcare provider may change your dose, temporarily stop, or completely stop your treatment with NUBEQA if you have certain side effects.
- Take your prescribed dose of NUBEQA 2 times a day with food.
- Swallow NUBEQA tablets whole.
- If you are receiving gonadotropin-releasing hormone (GnRH) therapy, you should continue with this treatment during your treatment with NUBEQA unless you have had a surgery to lower the amount of testosterone in your body (surgical castration).
- If you miss a dose of NUBEQA, take your prescribed dose as soon as you remember before the next scheduled dose. Do not take 2 doses together to make up for a missed dose.
- If you take more NUBEQA than prescribed, call your healthcare provider right away.

What are the possible side effects of NUBEQA?
NUBEQA may cause serious side effects, including:

- Heart disease. Blockage of the arteries in the heart (ischemic heart disease) that can lead to death has happened in some people during treatment with NUBEQA. Your healthcare provider will monitor you for signs and symptoms of heart problems during your treatment with NUBEQA. Call your healthcare provider or get medical help right away if you get chest pain or discomfort at rest or with activity, or shortness of breath during your treatment with NUBEQA.
- Seizure. Treatment with NUBEQA may increase your risk of having a seizure. You should avoid activities where a sudden loss of consciousness could cause serious harm to yourself or others. Tell your healthcare provider right away if you have loss of consciousness or seizure during treatment with NUBEQA.

The most common side effects of NUBEQA include:

- increase in liver function tests
- decreased white blood cells (neutropenia)
- feeling more tired than usual

The most common side effects of NUBEQA in combination with docetaxel include:

- constipation
- rash
- decreased appetite
- bleeding
- weight gain
- high blood pressure

- decreased red blood cells (anemia)
- high blood sugar levels
- decreased white blood cells
- increase in liver function tests
- low blood calcium levels

NUBEQA may cause fertility problems in males, which may affect the ability to father children. Talk to your healthcare provider if you have concerns about fertility.
These are not all the possible side effects of NUBEQA.
Call your healthcare provider for medical advice about side effects. You may report side effects to FDA at 1-800-FDA-1088.

How should I store NUBEQA?

- Store NUBEQA at room temperature between 68°F to 77°F (20°C to 25°C).
- Keep the bottle tightly closed after you first open it.

Keep NUBEQA and all medicines out of the reach of children.

General information about the safe and effective use of NUBEQA.
Medicines are sometimes prescribed for purposes other than those listed in a Patient Information leaflet. Do not use NUBEQA for a condition for which it was not prescribed. Do not give NUBEQA to other people, even if they have the same symptoms that you have. It may harm them. You can ask your healthcare provider or pharmacist for information about NUBEQA that is written for health professionals.

What are the ingredients in NUBEQA?
Active ingredient: darolutamide
Inactive ingredients: calcium hydrogen phosphate, croscarmellose sodium, lactose monohydrate, magnesium stearate, povidone K 30, hypromellose 15 cP, macrogol 3350, and titanium dioxide.
Manufactured by: Orion Corporation, Orion Pharma, FI-02101 Espoo, Finland
Manufactured for: Bayer HealthCare Pharmaceuticals Inc., Whippany, NJ 07981 USA
© 2019 Bayer HealthCare Pharmaceuticals Inc.
For more information, call Bayer HealthCare Pharmaceuticals Inc. at Bayer at 1-888-842-2937 or go to www.NUBEQA-us.com

This Patient Information has been approved by the U.S. Food and Drug Administration.

Revised: 6/2025

PACKAGE/LABEL PRINCIPAL DISPLAY PANEL

50419-395-01

Rx Only

NUBEQA

(darolutamide) tablets

300 mg

120 film-coated tablets